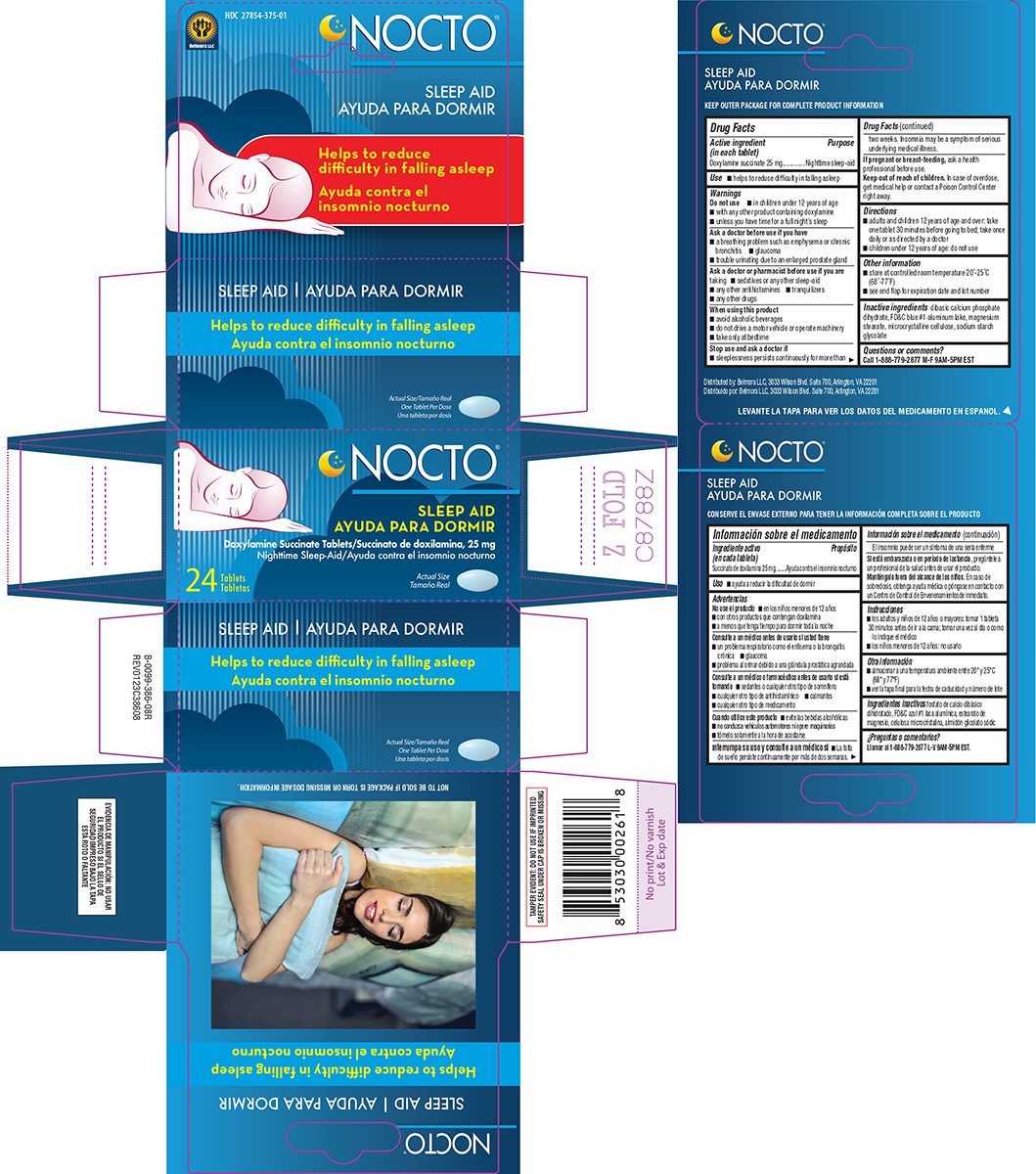 DRUG LABEL: Nocto Sleep Aid
NDC: 27854-375 | Form: TABLET
Manufacturer: Belmora LLC
Category: otc | Type: HUMAN OTC DRUG LABEL
Date: 20250719

ACTIVE INGREDIENTS: DOXYLAMINE SUCCINATE 25 mg/1 1
INACTIVE INGREDIENTS: DIBASIC CALCIUM PHOSPHATE DIHYDRATE; FD&C BLUE NO. 1 ALUMINUM LAKE; MAGNESIUM STEARATE; MICROCRYSTALLINE CELLULOSE; SODIUM STARCH GLYCOLATE TYPE A POTATO

Nocto 44-386

Active ingredient (in each tablet)

Doxylamine succinate 25 mg

Purpose

Nighttime sleep-aid

Use

- helps to reduce difficulty in falling asleep

Warnings

Do not use

- in children under 12 years of age
- with any other product containing doxylamine
- unless you have time for a full night’s sleep

Ask a doctor before use if you have

- a breathing problem such as emphysema or chronic bronchitis
- trouble urinating due to an enlarged prostate gland
- glaucoma

Ask a doctor or pharmacist before use if you are

taking

- sedatives or any other sleep-aid
- tranquilizers
- any other antihistamines
- any other drugs

When using this product

- avoid alcoholic beverages
- do not drive a motor vehicle or operate machinery
- take only at bedtime

Stop use and ask a doctor if

- sleeplessness persists continuously for more than two weeks. Insomnia may be a symptom of serious underlying medical illness.

If pregnant or breast-feeding,

ask a health professional before use.

Keep out of reach of children.

In case of overdose, get medical help or contact a Poison Control Center right away.

Directions

- adults and children 12 years of age and over: take one tablet 30 minutes before going to bed; take once daily or as directed by a doctor
- children under 12 years of age: do not use

Other information

- store at controlled room temperature 20°-25°C (68°-77°F)
- see end flap for expiration date and lot number

Inactive ingredients

dibasic calcium phosphate dihydrate, FD&C blue #1 aluminum lake, magnesium stearate, microcrystalline cellulose, sodium starch glycolate

Questions or comments?

Call 1-888-779-2877 M-F 9AM-5PM EST

Principal display panel

Belmora LLC

NDC 27854-375-01

NOCTO®

SLEEP AID
Doxylamine Succinate Tablets 25 mg
Nighttime Sleep-Aid

Helps to reduce
difficulty in falling asleep

24 Tablets

Actual Size
One Tablet Per Dose

TAMPER EVIDENT: DO NOT USE IF IMPRINTED
SAFETY SEAL UNDER CAP IS BROKEN OR MISSING

NOT TO BE SOLD IF PACKAGE IS TORN OR MISSING DOSAGE INFORMATION.

Distributed by: Belmora LLC, 3033 Wilson Blvd. Suite 700, Arlington, VA 22201

Nocto 44-386